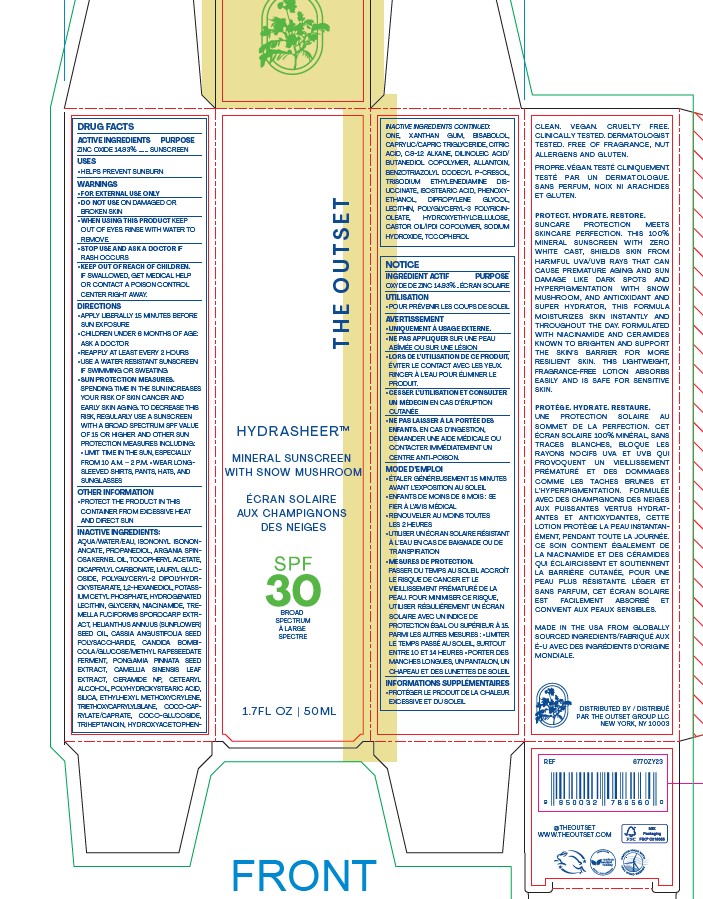 DRUG LABEL: HYDRASHEER MINERAL SUNSCREEN
NDC: 84436-0001 | Form: LOTION
Manufacturer: THE OUTSET GROUP LLC
Category: otc | Type: HUMAN OTC DRUG LABEL
Date: 20260107

ACTIVE INGREDIENTS: ZINC OXIDE 149.3 mg/1 mL
INACTIVE INGREDIENTS: DIPROPYLENE GLYCOL; SODIUM HYDROXIDE; POLYGLYCERYL-2 DIPOLYHYDROXYSTEARATE; NIACINAMIDE; TRIETHOXYCAPRYLYLSILANE; ISOSTEARIC ACID; TOCOPHEROL; 1,2-HEXANEDIOL; POLYHYDROXYSTEARIC ACID (2300 MW); ALLANTOIN; WATER; ISONONYL ISONONANOATE; PONGAMIA PINNATA SEED; CERAMIDE NP; TRISODIUM ETHYLENEDIAMINE DISUCCINATE; GLYCERIN; LAURYL GLUCOSIDE; POTASSIUM CETYL PHOSPHATE; ETHYLHEXYL METHOXYCRYLENE; ARGANIA SPINOSA SEED; BENZOTRIAZOLYL DODECYL P-CRESOL; PHENOXYETHANOL; PROPANEDIOL; DICAPRYLYL CARBONATE

ACTIVE INGREDIENTS
ZINC OXIDE 14.93% …

PURPOSE
..... SUNSCREEN

USES

- HELPS PREVENT SUNBURN

WARNINGS
• FOR EXTERNAL USE ONLY
• DO NOT USE ON DAMAGED OR
BROKEN SKIN
• WHEN USING THIS PRODUCT KEEP
OUT OF EYES. RINSE WITH WATER TO
REMOVE.
• STOP USE AND ASK A DOCTOR IF
RASH OCCURS

KEEP OUT OF REACH OF CHILDREN.
IF SWALLOWED, GET MEDICAL HELP
OR CONTACT A POISON CONTROL
CENTER RIGHT AWAY.

DIRECTIONS
• APPLY LIBERALLY 15 MINUTES BEFORE SUN EXPOSURE
• CHILDREN UNDER 6 MONTHS OF AGE ASK A DOCTOR
• REAPPLY AT LEAST EVERY 2 HOURS
• USE A WATER RESISTANT SUNSCREEN IF SWIMMING OR SWEATING
• SUN PROTECTION MEASURES.
SPENDING TIME IN THE SUN INCREASES YOUR RISK OF SKIN CANCER AND EARLY SKIN AGING. TO DECREASE THIS
RISK, REGULARLY USE A SUNSCREEN WITH A BROAD SPECTRUM SPF VALUE OF 15 OR HIGHER AND OTHER SUN
PROTECTION MEASURES INCLUDING
• LIMIT TIME IN THE SUN, ESPECIALLY
FROM 10 A.M. - 2 P.M. • WEAR LONG SLEEVED SHIRTS, PANTS, HATS, AND SUNGLASSES

OTHER INFORMATION
• PROTECT THE PRODUCT IN THIS
CONTAINER FROM EXCESSIVE HEAT
AND DIRECT SUN

INACTIVE INGREDIENTS
AQUA/WATER/EAU, ISONONYL ISONONANOATE, PROPANEDIOL, ARGANIA SPINOSA KERNEL OIL, TOCOPHERYL ACETATE, DICAPRYLYL CARBONATE, LAURYL GLUCOSIDE, POLYGLYCERYL-2 DIPOLYHYDROXYSTEARATE, 1,2-HEXANEDIOL, POTASSIUM CETYL PHOSPHATE, HYDROGENATED LECITHIN, GLYCERIN, NIACINAMIDE, TREMELLA FUCIFORMIS SPOROCARP EXTRACT, HELIANTHUS ANNUUS SUNFLOWER SEED OIL, CASSIA ANGUSTIFOLIA SEED POLYSACCHARIDE, CANDIDA BOMBICOLA/GLUCOSE/METHYL RAPESEEDATE FERMENT, PONGAMIA PINNATA SEED EXTRACT, CAMELLIA SINENSIS LEAF EXTRACT, CERAMIDE NP, CETEARYL ALCOHOL, POLYHYDROXYSTEARIC ACID, SILICA, ETHYLHEXYL METHOXYCRYLENE, TRIETHOXYCAPRYLYLSILANE, COCO-CAPRYLATE CAPRATE, COCO-GLUCOSIDE, TRIHEPTANOIN, HYDROXYACETOPHENONE, XANTHAN GUM, BISABOLOL,CAPRYLIC/CAPRIC TRIGLYCERIDE, CITRIC ACID, C9-12 ALKANE, DILINOLEIC ACID BUTANEDIOL COPOLYMER, ALLANTOIN, BENZOTRIAZOLYL DODECYL P-CRESOL, TRISODIUM ETHYLENEDIAMINE DISUCCINATE, ISOSTEARIC ACID, PHENOXYETHANOL, DIPROPYLENE GLYCOL, LECITHIN, POLYGLYCERYL-3 POLYRICINOLEATE, HYDROXYETHYLCELLULOSE, CASTOR OIL IPDI COPOLYMER, SODIUM HYDROXIDE, TOCOPHEROL